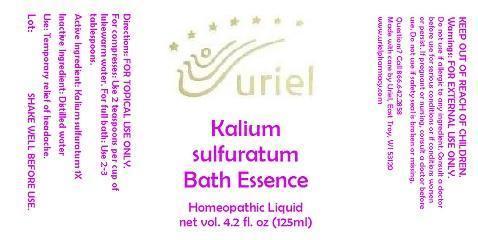 DRUG LABEL: Kali Sulf. Bath Essence
NDC: 48951-6005 | Form: LIQUID
Manufacturer: Uriel Pharmacy Inc.
Category: homeopathic | Type: HUMAN OTC DRUG LABEL
Date: 20140806

ACTIVE INGREDIENTS: POTASSIUM SULFIDE 1 [hp_X]/1 mL
INACTIVE INGREDIENTS: WATER

Kali Sulf. Bath Essence

INDICATIONS AND USAGE

Directions: FOR TOPICAL USE ONLY. SHAKE WELL BEFORE USE.

DOSAGE AND ADMINISTRATION

For compresses: Use 2 teaspoons per cup of lukewarm water. For full bath: Use 2-3 tablespoons.

Active Ingredient: Kalium sulfuratum 1X

Inactive Ingredient: Distilled water

PURPOSE

Use: Temporary relief of headache.

KEEP OUT OF REACH OF CHILDREN.

WARNINGS

Warnings: FOR EXTERNAL USE ONLY. Do not use if allergic to any ingredient. Consult a doctor before use for serious conditions or if conditions worsen or persist. If pregnant or nursing, consult a doctor before use. Do not use if safety seal is broken or missing.

QUESTIONS

Questions? Call 866.642.2858 Made with care by Uriel, East Troy, WI 53120 www.urielpharmacy.com